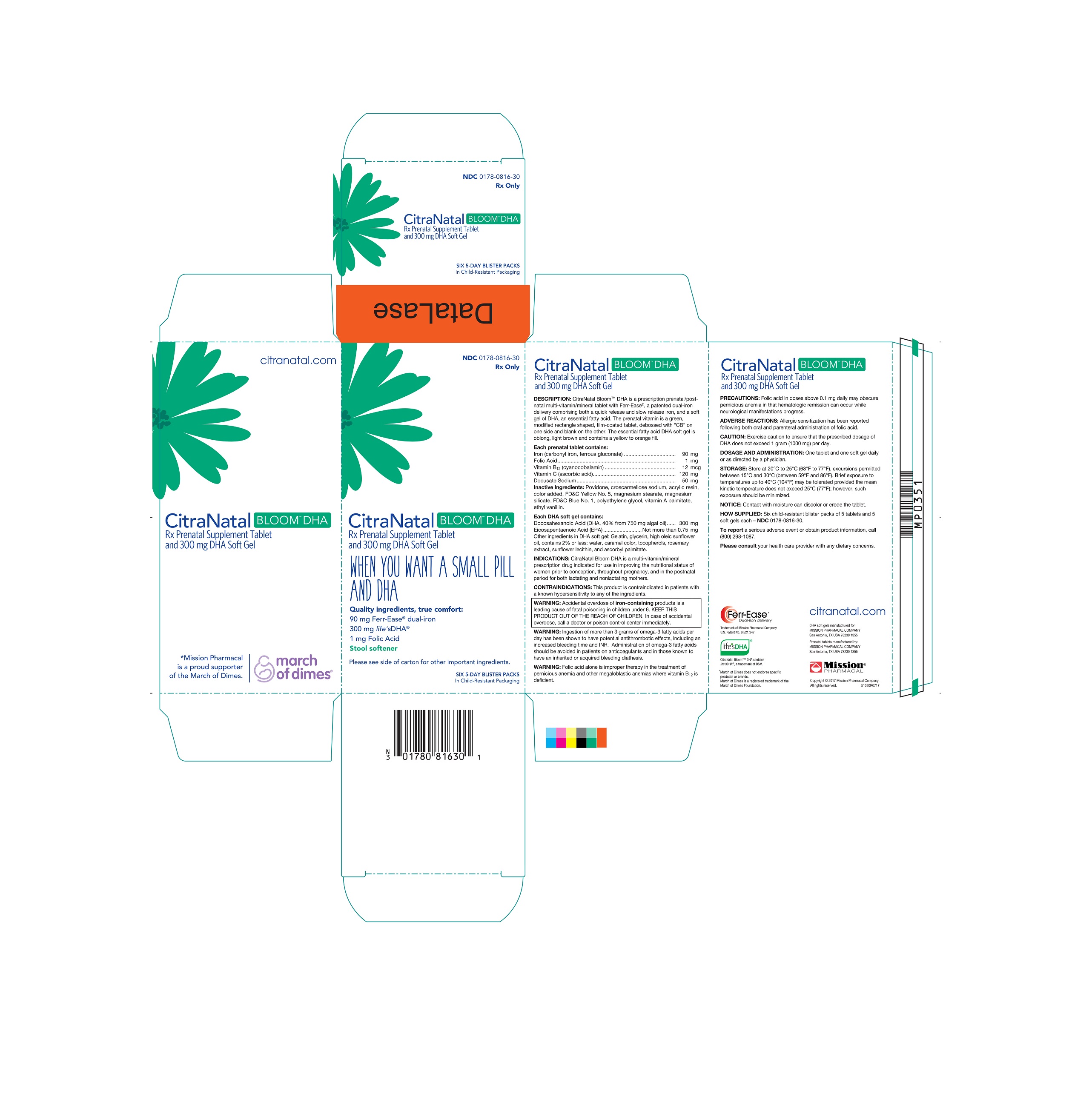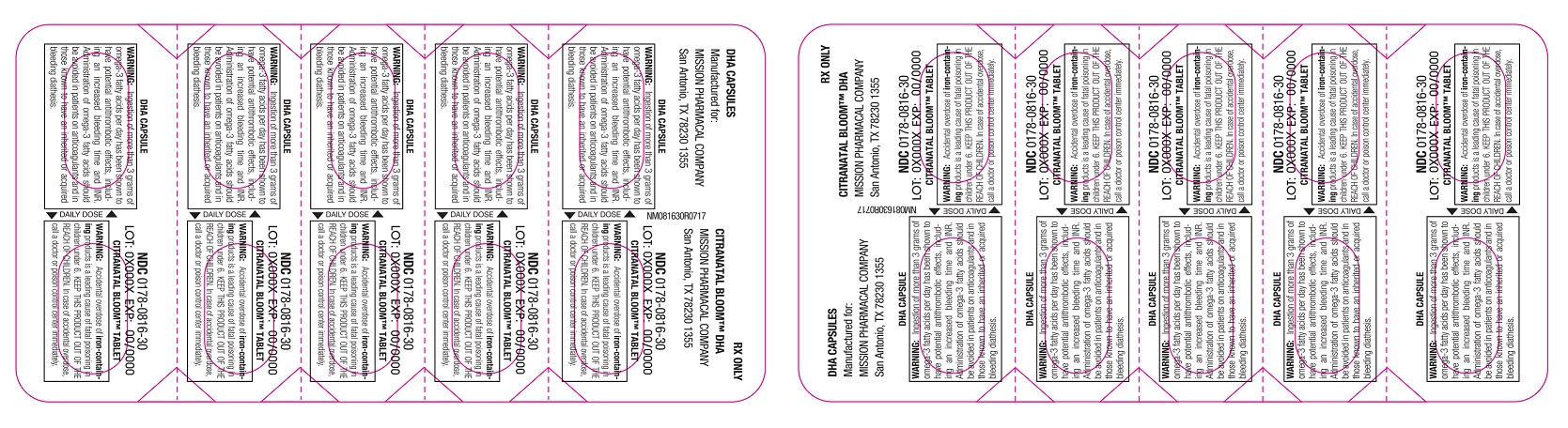 DRUG LABEL: CitraNatal Bloom DHA
NDC: 0178-0816 | Form: KIT | Route: ORAL
Manufacturer: Mission Pharmacal Company
Category: prescription | Type: HUMAN PRESCRIPTION DRUG LABEL
Date: 20200406

ACTIVE INGREDIENTS: ASCORBIC ACID 120 mg/1 1; FOLIC ACID 1 mg/1 1; CYANOCOBALAMIN 12 ug/1 1; FERROUS GLUCONATE 1.5 mg/1 1; IRON PENTACARBONYL 88.5 mg/1 1; DOCUSATE SODIUM 50 mg/1 1; CRYPTHECODINIUM COHNII DHA OIL 300 mg/300 mg
INACTIVE INGREDIENTS: MAGNESIUM SILICATE; VITAMIN A PALMITATE; ETHYL VANILLIN; FD&C BLUE NO. 1; POLYETHYLENE GLYCOL 8000; FD&C YELLOW NO. 5; MAGNESIUM STEARATE; TITANIUM DIOXIDE; DIMETHYLAMINOETHYL METHACRYLATE - BUTYL METHACRYLATE - METHYL METHACRYLATE COPOLYMER; POVIDONE; ICOSAPENT; SUNFLOWER OIL; ROSEMARY; ASCORBYL PALMITATE; LECITHIN, SUNFLOWER; TOCOPHEROL

CitraNatal Bloom DHA
Rx Prenatal Vitamin Tablet and 300 mg DHA Capsule

DESCRIPTION

CitraNatal Bloom™ DHA is a prescription prenatal/postnatal multi-vitamin/mineral tablet with Ferr-Ease®, a patented dual-iron delivery comprising both a quick release and slow release iron, and a soft gel of DHA, an essential fatty acid. The prenatal vitamin is a green, modified rectangle shaped, film-coated tablet, debossed with “CB” on one side and blank on the other. The essential fatty acid DHA soft gel is oblong, light brown and contains a yellow to orange fill.

Each prenatal tablet contains:

Iron (Carbonyl iron, ferrous gluconate)...........................90 mg

Folic Acid .........................................................................1 mg

Vitamin B12 (Cyanocobalamin) ...................................12 mcg

Vitamin C (Ascorbic acid).............................................120 mg

Docusate sodium ..........................................................50 mg

INACTIVE INGREDIENT

Povidone, croscarmellose sodium, acrylic resin, color added, FD&C Yellow No. 5, magnesium stearate, magnesium silicate, FD&C Blue No. 1, polyethylene glycol, vitamin A palmitate, ethyl vanillin.

INDICATIONS AND USAGE

CitraNatal Bloom DHA is a multi-vitamin/mineral prescription drug indicated for use in improving the nutritional status of women prior to conception, throughout pregnancy, and in the postnatal period for both lactating and nonlactating mothers.

WARNINGS AND PRECAUTIONS

WARNING: Accidental overdose of iron-containing products is a leading cause of fatal poisoning in children under 6. KEEP THIS PRODUCT OUT OF THE REACH OF CHILDREN. In case of accidental overdose, call a doctor or poison control center immediately.

WARNING: Ingestion of more than 3 grams of omega-3 fatty acids per day has been shown to have potential antithrombotic effects, including an increased bleeding time and INR. Administration of omega-3 fatty acids should be avoided in patients on anticoagulants and in those known to have an inherited or acquired bleeding diathesis.

WARNING: Folic acid alone is improper therapy in the treatment of pernicious anemia and other megaloblastic anemias where vitamin B12 is deficient.

PRECAUTIONS: Folic acid in doses above 0.1 mg daily may obscure pernicious anemia in that hematologic remission can occur while neurological manifestations progress.

CAUTION: Exercise caution to ensure that the prescribed dosage of DHA does not exceed 1 gram (1000 mg) per day.

Please consult your health care provider with any dietary concerns.

ADVERSE REACTIONS

Allergic sensitization has been reported following both oral and parenteral administration of folic acid.

DOSAGE AND ADMINISTRATION

One tablet and one soft gel daily or as directed by a physician.

STORAGE AND HANDLING

STORAGE: Store at 20°C to 25°C (68°F to 77°F), excursions permitted between 15°C and 30°C (between 59°F and 86°F). Brief exposure to temperatures up to 40°C (104°F) may be

tolerated provided the mean kinetic temperature does not exceed 25°C (77°F); however, such exposure should be minimized.

NOTICE: Contact with moisture can discolor or erode the tablet.

HOW SUPPLIED

Six child-resistant blister packs of 5 tablets and 5 soft gels each – NDC 0178-00816-30.

To report a serious adverse event or obtain product information, call (800) 298-1087.

MISSION PHARMACAL COMPANY, San Antonio, TX 78230 1355

51080R0717

MISSION® PHARMACAL

DHA capsules manufactured for:
MISSION PHARMACAL COMPANY
San Antonio, TX USA 78230 1355
Prenatal tablets manufactured by:
MISSION PHARMACAL COMPANY
San Antonio, TX USA 78230 1355

Copyright © 2017 Mission Pharmacal Company.

All rights reserved.
www.missionpharmacal.com

Ferr-Ease ®
Dual-iron delivery

Trademark of Mission Pharmacal Company
U.S. Patent No. 6,521,247

life's DHA ®

life’sDHA is a trademark of DSM.
U.S. Patent No. 7,579,174
U.S. Patent No. 7,732,170
U.S. Patent No. 5,518,918

*March of Dimes does not endorse
specific products or brands.
March of Dimes is a registered trademark
of the March of Dimes Foundation.

PACKAGE LABEL

Six child-resistant blister packs of 5 tablets and 5 capsules each - NDC 0178-0816-30

PACKAGE LABEL

Retail Carton